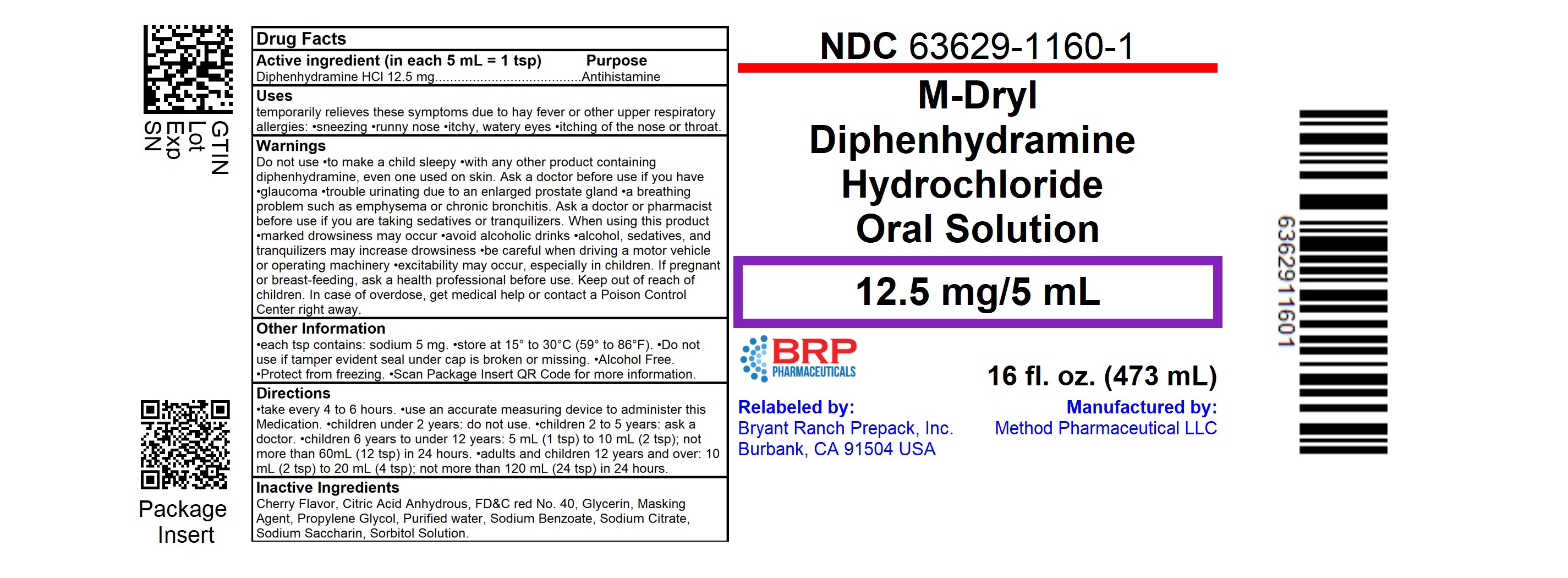 DRUG LABEL: M-Dryl
NDC: 72162-1674 | Form: LIQUID
Manufacturer: Bryant Ranch Prepack
Category: otc | Type: HUMAN OTC DRUG LABEL
Date: 20251118

ACTIVE INGREDIENTS: DIPHENHYDRAMINE HYDROCHLORIDE 12.5 mg/5 mL
INACTIVE INGREDIENTS: ANHYDROUS CITRIC ACID; FD&C RED NO. 40; GLYCERIN; PROPYLENE GLYCOL; WATER; SODIUM BENZOATE; SODIUM CITRATE, UNSPECIFIED FORM; SACCHARIN SODIUM; SORBITOL

M-Dryl

M-Dryl

Diphenhydramine Hydrochloride Oral Solution

Antihistamine

Cherry Flavor

RELIEVES

- Sneezing
- Itchy, Watery Eyes
- Runny Nose
- Itchy Throat due to Allergies

DO NOT USE IF TAMPER EVIDENT SEAL

UNDER CAP IS BROKEN OR MISSING

Alcohol Free

Each 5 mL (1 teaspoonful) contains:

Diphenhydramine HCl ................ 12.5 mg

Drug Facts

Active ingredient

(in each 5 mL = 1 tsp)

Diphenhydramine HCl ..................................................... 12.5 mg

Uses

- temporarily relieves these symptoms due to hay fever or other upper respiratory allergies:
- sneezing
- runny nose
- itchy, watery eyes
- itching of the nose or throat

Warnings

Do not use

- to make a child sleepy
- with any other product containing diphenhydramine, even one used on skin

Ask a doctor before use if you have

- glaucoma
- trouble urinating due to an enlarged prostate gland
- a breathing problem such as emphysema or chronic bronchitis

Ask a doctor or pharmacist before use if you are

taking sedatives or tranquilizers.

When using this product

- marked drowsiness may occur
- avoid alcoholic drinks
- alcohol, sedatives, and tranquilizers may increase drowsiness
- be careful when driving a motor vehicle or operating machinery
- excitability may occur, especially in children

If pregnant or breast-feeding,

ask a health professional before use.

Keep out of reach of children.

In case of overdose, get medical help or contact a Poison Control Center right away.

Directions

- take every 4 to 6 hours
- use an accurate measuring device to administer this Medication

children under 2 years do not use | do not use
children 2 to 5 years | ask a doctor
children 6 years to under 12 years | 5 mL (1 tsp) to 10 mL (2 tsp); not more than 60 mL (12 tsp) in 24 hours
adults and children 12 years and over | 10 mL (2 tsp) to 20 mL (4 tsp); not more than 120 mL (24 tsp) in 24 hours

Other information

- each tsp contains: sodium 5 mg
- store at 15° to 30°C (59° to 86°F)

protect from freezing

Inactive ingredients

Cherry Flavor, Citric Acid Anhydrous, FD&C red No. 40, Glycerin, Masking Agent, Propylene Glycol, Purified water, Sodium Benzoate, Sodium Citrate, Sodium Saccharin, Sorbitol Solution.

Questions?

Serious side effects associated with use of this product may be reported to this number. Call 1-877-250-3427 Mon. - Fri. (8 a.m. to 5 p.m. CST).

HOW SUPPLIED

M-Dryl

Diphenhydramine Hydrochloride Oral Solution

NDC: 72162-1674-4: 473 mL in a BOTTLE

NDC: 72162-1674-2: 120 mL in a BOTTLE

Repackaged/Relabeled by:
Bryant Ranch Prepack, Inc. Burbank, CA 91504

PACKAGE LABEL

M-Dryl Oral Liquid 12.5 MG/5ML